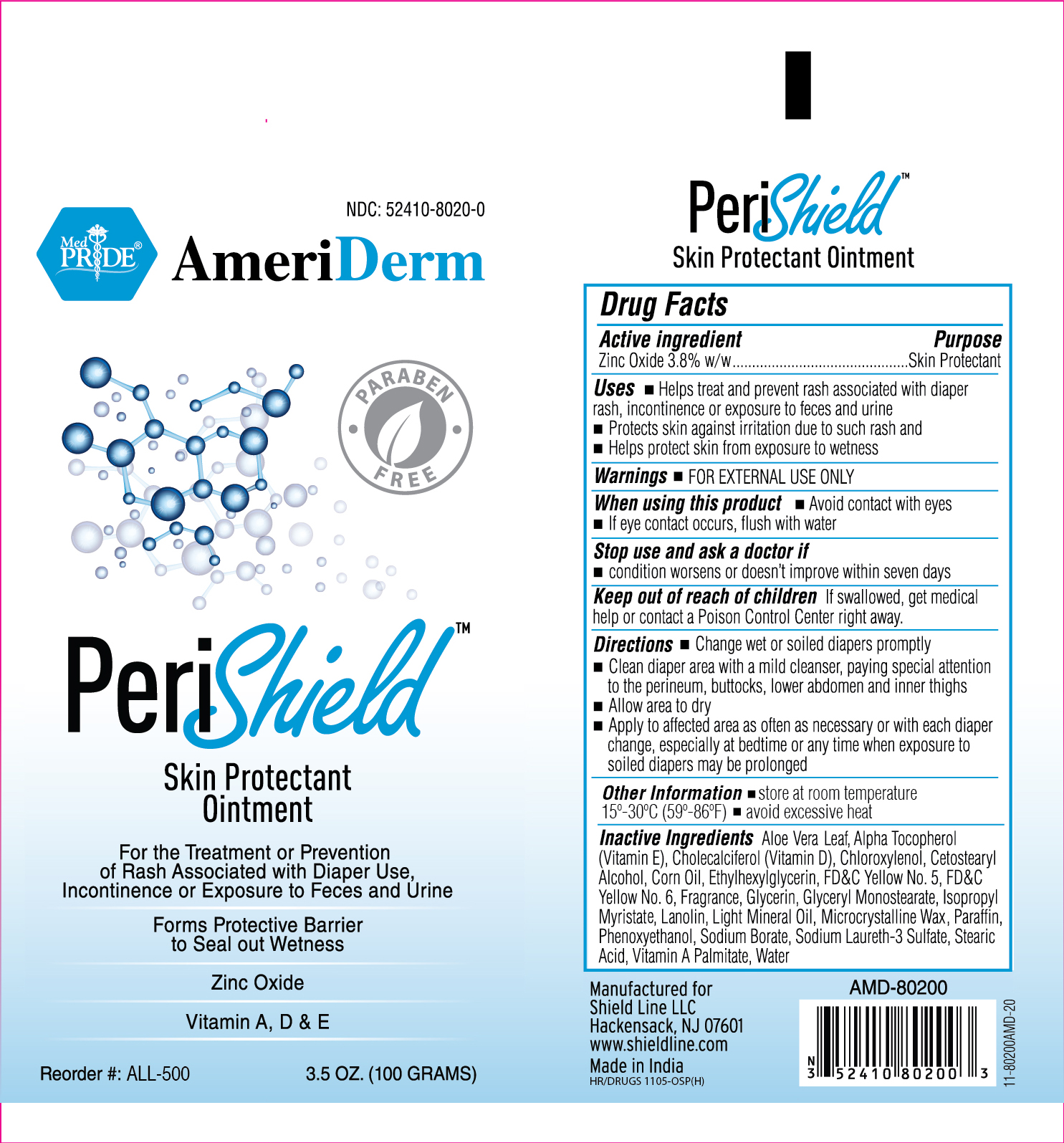 DRUG LABEL: AmeriDerm
NDC: 52410-8020 | Form: OINTMENT
Manufacturer: Shield Line LLC
Category: otc | Type: HUMAN OTC DRUG LABEL
Date: 20250815

ACTIVE INGREDIENTS: ZINC OXIDE 3.8 g/100 g
INACTIVE INGREDIENTS: FD&C YELLOW NO. 5; GLYCERYL MONOSTEARATE; ALOE VERA LEAF; CHLOROXYLENOL; CHOLECALCIFEROL; CORN OIL; LANOLIN; MINERAL OIL; PARAFFIN; PHENOXYETHANOL; VITAMIN A PALMITATE; SODIUM BORATE; ALPHA-TOCOPHEROL; ETHYLHEXYLGLYCERIN; SODIUM LAURETH-3 SULFATE; STEARIC ACID; GLYCERIN; CETOSTEARYL ALCOHOL; MICROCRYSTALLINE WAX; ISOPROPYL MYRISTATE; WATER; FD&C YELLOW NO. 6

PeriShield

Active Ingredient

Zinc Oxide 3.8%

Purpose

Skin Protectant

Uses

■ Helps treat and prevent rash associated with diaper rash,incontinence or exposure to feces and urine ■ Protects skin against irritation due to such rash and ■ Helps protect skin from exposure to wetness

Warnings

For external use only

When using this product

■ Avoid contact with eyes ■ If eye contact, occurs, flush with water

Stop Use and ask a doctor if

■ condition worsens or doesn't improve within seven days

Keep out of reach of children

If swallowed, get medical help or contact a Poison Control Center right away.

Directions

■ Change wet and soiled diapers promptly ■ Clean diaper area with a mild cleanser, paying special attention to the perineum, buttocks,lower abdomen and inner thighs ■ Allow area to dry ■ Apply to affected area as often as necessary or with each diaper change, especially at bedtime or anytime when exposure to soiled diapers may be prolonged

Inactive ingredients

Aloe Barbadensis Gel, Alpha Tocopherol (Vitamin E), Cholecalciferol (Vitamin D), Chloroxylenol, Cetostearyl Alcohol, Corn Oil, Ethylhexylglycerin, FD&C Yellow No. 5, FD&C Yellow No. 6, Fragrance, Glycerin, Glyceryl Monostearate, Isopropyl Myristate, Lanolin, Microcrystalline wax, Mineral Oil, Paraffin, Phenoxyethanol, Sodium Borate, Sodium Laureth-3 Sulfate, Stearic Acid, Vitamin A Palmitate, Water